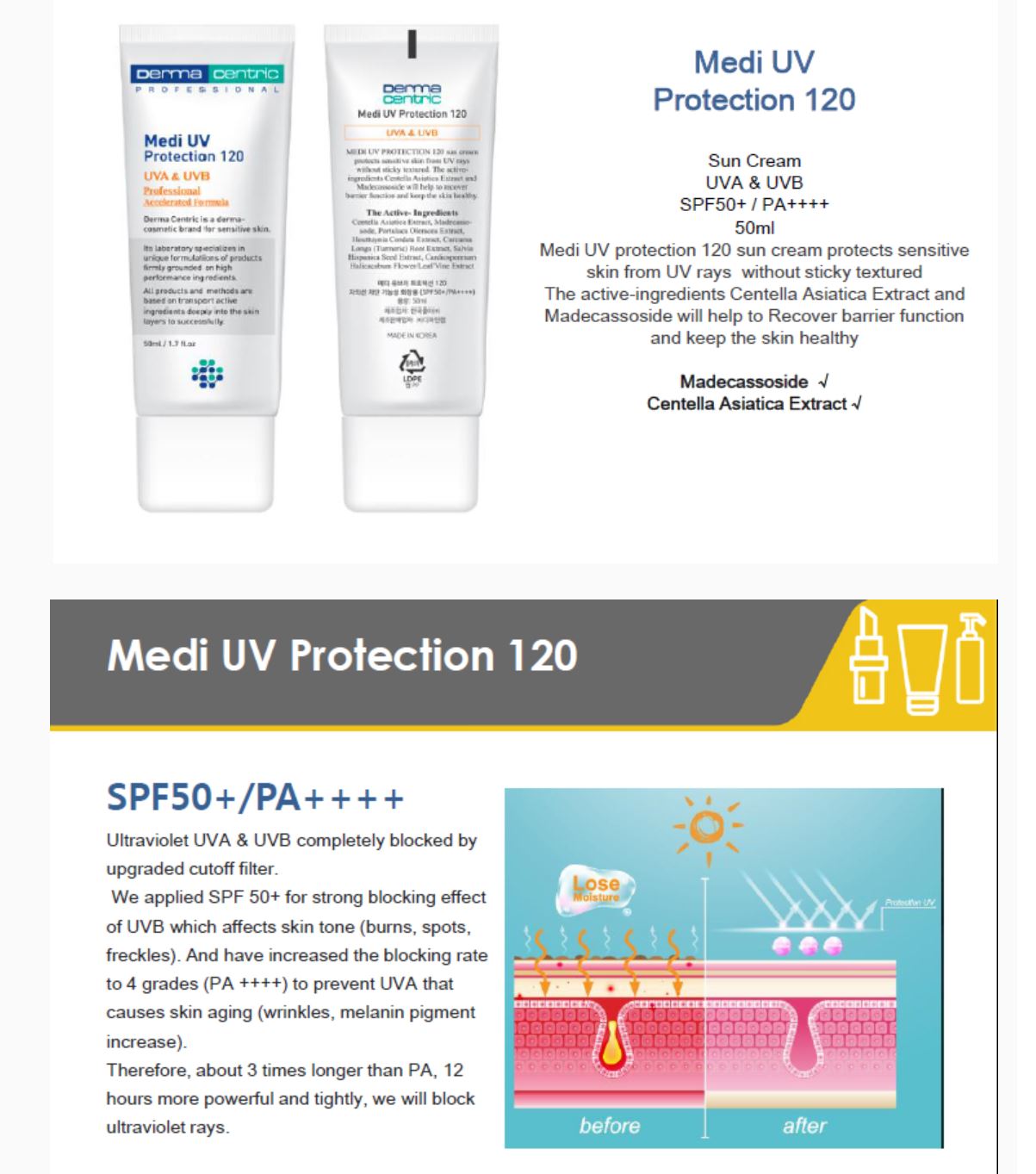 DRUG LABEL: MEDI UV PROTECTION 120
NDC: 79593-0003 | Form: SHAMPOO
Manufacturer: DERMA CENTRIC INC
Category: otc | Type: HUMAN OTC DRUG LABEL
Date: 20200808

ACTIVE INGREDIENTS: TITANIUM DIOXIDE 3 g/100 mL
INACTIVE INGREDIENTS: PROPANEDIOL; WATER; GLYCERIN; DIMETHICONE

ACTIVE INGREDIENT

titanium dioxide

PURPOSE

UV protection

KEEP OUT OF REACH OF THE CHILDREN

WARNINGS

■ For external use only.

■ Do not use in eyes.

■ lf swallowed, get medical help promptly.

■ Stop use, ask doctor lf irritation occurs.

■ Keep out of reach of children.

DOSAGE AND ADMINISTRATION

for external use only

INACTIVE INGREDIENT

WATER
ZINC OXIDE
CYCLOPENTASILOXANE
ETHYLHEXYL METHOXYCINNAMATE
DIMETHICONE
ETHYLHEXYL SALICYLATE
COCO-CAPRYLATE/CAPRATE
GLYCERIN
BUTYLOCTYL SALICYLATE
LAURYL PEG-10 TRIS(TRIMETHYLSILOXY)SILYLETHYL DIMETHICON
DIPROPYLENE GLYCOL
CAPRYLYL METHICONE
SILICA
ECHIUM PLANTAGINEUM SEED OIL
PORTULACA OLERACEA EXTRACT
CENTELLA ASIATICA EXTRACT
HOUTTUYNIA CORDATA EXTRACT
CURCUMA LONGA (TURMERIC) ROOT EXTRACT
SALVIA HISPANICA SEED EXTRACT
CARDIOSPERMUM HALICACABUM FLOWER/LEAF/VINE EXTRACT
LAURYL PEG-9 POLYDIMETHYLSILOXYETHYL DIMETHICONE
DISTEARDIMONIUM HECTORITE
MAGNESIUM SULFATE
METHYL METHACRYLATE CROSSPOLYMER
VINYL DIMETHICONE/METHICONE SILSESQUIOXANE CROSSPOLYMER
POLYGLYCERYL-6 POLYRICINOLEATE
PROPANEDIOL
ALUMINUM HYDROXIDE
TRIETHOXYCAPRYLYLSILANE
ALUMINUM STEARATE
CAPRYLYL GLYCOL
OCTYLDODECANOL
CETEARYL DIMETHICONE CROSSPOLYMER
GLYCERYL CAPRYLATE
SACCHARIDE HYDROLYSATE
ETHYLHEXYLGLYCERIN
MICROCRYSTALLINE CELLULOSE
1,2-HEXANEDIOL
CELLULOSE GUM
MADECASSOSIDE
SODIUM HYALURONATE
HELIANTHUS ANNUUS (SUNFLOWER) SEED OIL UNSAPONIFIABLES
TOCOPHEROL
FRAGRANCE

INDICATIONS AND USAGE

apply proper amount to the skin